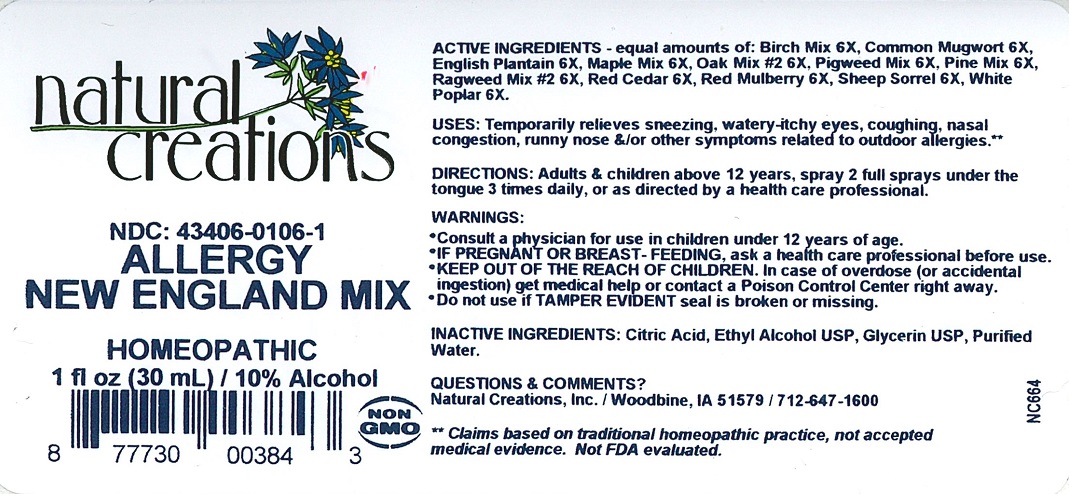 DRUG LABEL: ALLERGY NEW ENGLAND MIX
NDC: 43406-0106 | Form: LIQUID
Manufacturer: Natural Creations, Inc.
Category: homeopathic | Type: HUMAN OTC DRUG LABEL
Date: 20251113

ACTIVE INGREDIENTS: BETULA PUBESCENS BARK 6 [hp_X]/1 mL; ARTEMISIA VULGARIS POLLEN 6 [hp_X]/1 mL; PLANTAGO LANCEOLATA POLLEN 6 [hp_X]/1 mL; ACER PSEUDOPLATANUS POLLEN 6 [hp_X]/1 mL; EVERNIA PRUNASTRI 6 [hp_X]/1 mL; AMARANTHUS RETROFLEXUS POLLEN 6 [hp_X]/1 mL; PINUS MASSONIANA POLLEN 6 [hp_X]/1 mL; PINUS TABULIFORMIS POLLEN 6 [hp_X]/1 mL; AMBROSIA ARTEMISIIFOLIA POLLEN 6 [hp_X]/1 mL; JUNIPERUS VIRGINIANA POLLEN 6 [hp_X]/1 mL; MORUS RUBRA POLLEN 6 [hp_X]/1 mL; RUMEX ACETOSELLA POLLEN 6 [hp_X]/1 mL; POPULUS ALBA POLLEN 6 [hp_X]/1 mL
INACTIVE INGREDIENTS: ALCOHOL; CITRIC ACID ACETATE; GLYCERIN; WATER

ALLERGY NEW ENGLAND MIX

ACTIVE INGREDIENT

Active Ingredients - equal amounts of: Birch Mix 6X, Common Mugwort 6X, English Plantain 6X, Maple Mix, Oak Mix #2 6X, Pigweed Mix 6X, Pine Mix 6X, Ragweed Mix #2 6X, Red Cedar 6X, Red Mulberry 6X, Sheep Sorrel 6X, White Popular 6X.

PURPOSE

Uses: Temporarily relieves sneezing, watery-itchy eyes, coughing, nasal congestion, runny nose &/or other symptoms related to outdoor allergies**.

REFERENCES

** These statements have not been reviewed by the FDA. They are based on traditional homeopathic practice.

INDICATIONS AND USAGE

Uses: Temporarily relieves sneezing, watery-itchy eyes, coughing, nasal congestion, runny nose &/or other symptoms related to outdoor allergies.**

DOSAGE AND ADMINISTRATION

Directions: Adults & children above 12 years, spray 2 full sprays under the tongue 3 times daily, or as directed by a health care professional.

KEEP OUT OF REACH OF CHILDREN

IF PREGNANT OR BREAST-FEEDING, ask a health care professional before use.

KEEP OUT OF THE REACH OF CHILDREN. In case of overdose (or accidental ingestion) get

medical help or contact a Poison Control Center right away.

WARNINGS:

- Consult a physician for use in children under 12 years of age.
- IF PREGNANT OR BREAST-FEEDING, ask a health care professional before use.
- KEEP OUT OF THE REACH OF CHILDREN. In case of overdose (or accidental ingestion) get medical help or contact a Poison Control Center right away.
- Do not us if TAMPER EVIDENT seal is broken or missing.

INACTIVE INGREDIENT

Inactive Ingredients: Citric Acid, Ethyl Alcohol USP, Glycerin USP, Purified Water.

QUESTIONS

NDC: 43406-0106-1

ALLERGY NEW ENGLAND MIX

HOMEOPATHIC

1 FL OZ (30mL) / 10% Alcohol

PACKAGE LABEL

NDC: 43406-0106-1

ALLERGY

NEW ENGLAND MIX

HOMEOPATHIC

1 fl oz (30 mL)/10%